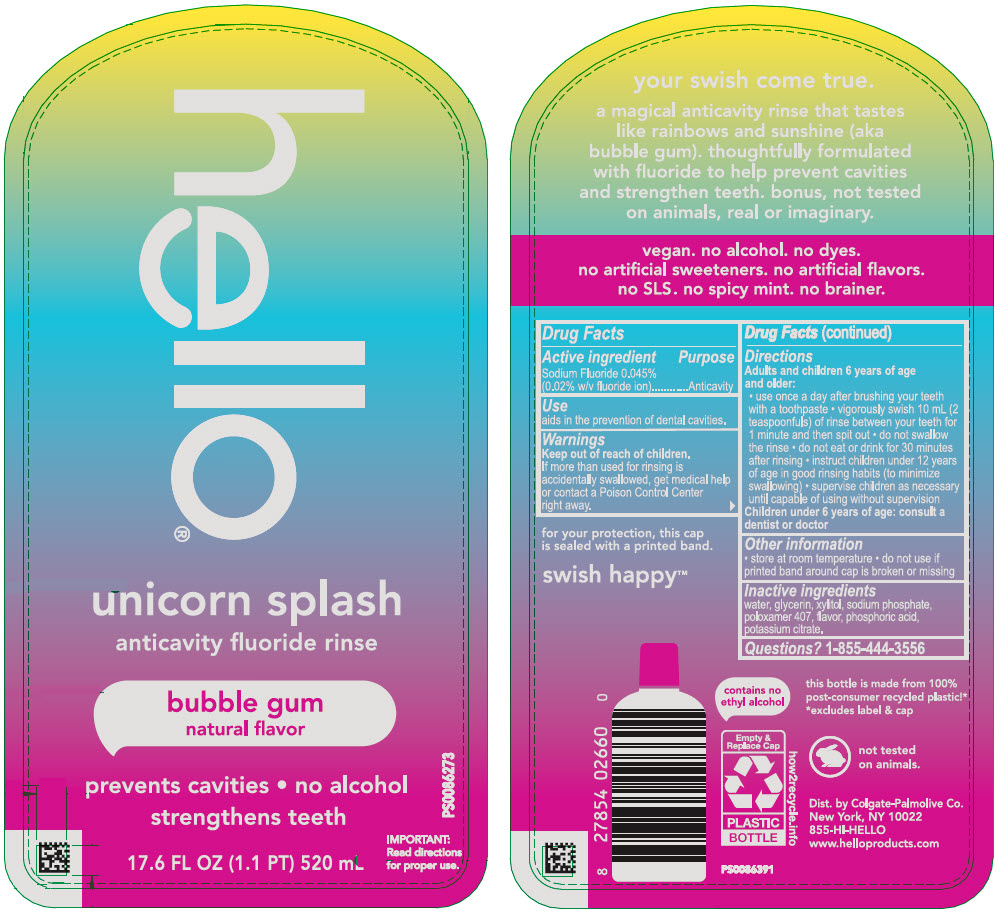 DRUG LABEL: Hello Unicorn Splash
NDC: 35000-687 | Form: MOUTHWASH
Manufacturer: Colgate-Palmolive Company
Category: otc | Type: HUMAN OTC DRUG LABEL
Date: 20251110

ACTIVE INGREDIENTS: SODIUM FLUORIDE 0.02 g/100 mL
INACTIVE INGREDIENTS: WATER; GLYCERIN; XYLITOL; SODIUM PHOSPHATE, MONOBASIC, ANHYDROUS; POLOXAMER 407; POTASSIUM CITRATE; PHOSPHORIC ACID

Hello® Unicorn Splash
unicorn splash anticavity fluoride rinse

Drug Facts

Active ingredient

Sodium Fluoride 0.05% (0.02% w/v fluoride ion)

Purpose

Anticavity

Use

aids in the prevention of dental cavities.

Warnings

Keep out of reach of children.

If more than used for rinsing is accidentally swallowed, get medical help or contact a Poison Control Center right away.

Directions

Adults and children 6 years of age and older:

- Use once a day after brushing your teeth with a toothpaste
- vigorously swith 10 mL (2 teaspoonfuls) of rinse between your teeth for 1 minute and then spit out
- do not swallow the rinse
- do not eat or drink for 30 minutes after rinsing
- instruct children under 12 years of age in good rinsing habits (to minimize swallowing)
- supervise children as necessary until capable of using without supervision

Children under 6 years of age: consult a dentist or doctor

Other information

- store at room temperature
- do not use if printed band around cap is broken or missing

Inactive ingredients

purified water, vegetable glycerin, xylitol, sodium phosphate monobasic, flavor, poloxamer 407, potassium citrate, phosphoric acid

Questions?

1-855-444-3556

Dist. by Colgate-Palmolive Co.
New York, NY 10022

PRINCIPAL DISPLAY PANEL - 520 mL Bottle Label

hello®

unicorn splash
anticavity fluoride rinse

bubble gum
natural flavor

prevents cavities • no alcohol
strengthens teeth

17.6 FL OZ (1.1 PT) 520 mL

PS0086273

IMPORTANT:
Read directions
for proper use.